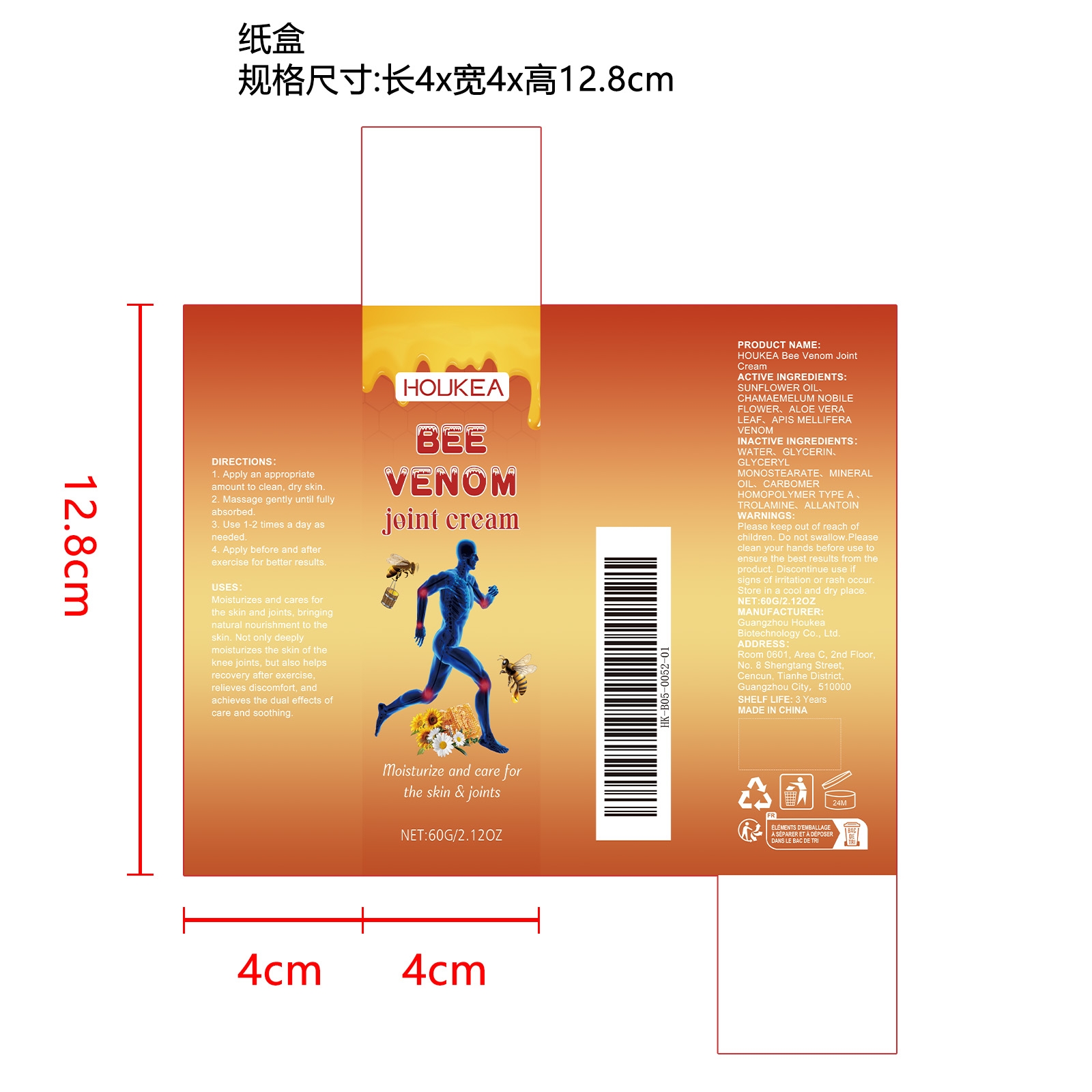 DRUG LABEL: HOUKEA Bee Venom Joint Cream
NDC: 84984-003 | Form: CREAM
Manufacturer: Guangzhou Houkea Biotechnology Co., Ltd.
Category: otc | Type: HUMAN OTC DRUG LABEL
Date: 20251127

ACTIVE INGREDIENTS: CHAMAEMELUM NOBILE FLOWER 0.012 mg/60 mg; ALOE VERA LEAF 0.012 mg/60 mg; SUNFLOWER OIL 0.012 mg/60 mg; APIS MELLIFERA VENOM 0.012 mg/60 mg
INACTIVE INGREDIENTS: GLYCERIN 4.8 mg/60 mg; MINERAL OIL 1.2 mg/60 mg; CARBOMER HOMOPOLYMER TYPE A 0.12 mg/60 mg; TROLAMINE 0.12 mg/60 mg; GLYCERYL MONOSTEARATE 1.2 mg/60 mg; WATER 52.5 mg/60 mg; ALLANTOIN 0.012 mg/60 mg

ACTIVE INGREDIENT

SUNFLOWER OIL、CHAMAEMELUM NOBILEFLOWER、ALOE VERA LEAF、APIS MELLIFERA VENOM

PURPOSE

Moisturizes and cares for the skin and joints, bringing natural nourishment to the skin. Not only deeply moisturizes the skin of the knee joints, but also helps recovery after exercise, relieves discomfort, and achieves the dual effects of care and soothing.

WHEN USING

1. Apply an appropriate amount to clean, dry skin.

2. Massage gently until fully absorbed.

3. Use 1-2 times a day as needed.

4. Apply before and after exercise for better results.

WARNINGS

Please keep out of reach of children. Do not swallow.Please clean your hands before use to ensure the best results from the product. Discontinue use if signs of irritation or rash occur. Store in a cool and dry place.

KEEP OUT OF REACH OF CHILDREN

Please keep out of reach of children. Do not swallow.

STOP USE

Discontinue use if signs of irritation or rash occur.

DO NOT USE

Discontinue use if signs of irritation or rash occur.

STORAGE AND HANDLING

Store in a cool and dry place.

INACTIVE INGREDIENT

WATER、
GLYCERIN
GLYCERYL MONOSTEARATE、
MINERAL OIL、
CARBOMER HOMOPOLYMER TYPE A、
TROLAMINE、
ALLANTOIN